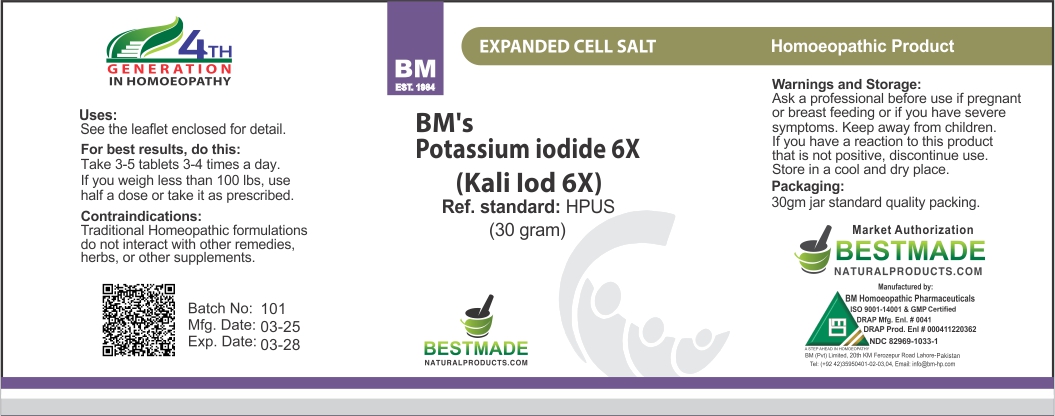 DRUG LABEL: Bestmade Natural Products Potassium Iodide (Kali Iod)
NDC: 82969-1033 | Form: TABLET, SOLUBLE
Manufacturer: Bestmade Natural Products
Category: homeopathic | Type: HUMAN OTC DRUG LABEL
Date: 20250526

ACTIVE INGREDIENTS: POTASSIUM IODIDE 6 [hp_X]/6 [hp_X]
INACTIVE INGREDIENTS: LACTOSE 6 [hp_X]/6 [hp_X]

Potassium lodide 6X
Kali lod 6x

DOSAGE AND ADMINISTRATION

For best results, do this:

Take 3-5 tablets 3-4 times a day.

If you weigh less than 100 lbs, use half a dose or take it as prescribed.

Contraindications:

Traditional Homeopathic formulations do not interact with other remedies, herbs, or other supplements.

Active Ingredients:
Kali lodatum 6X (HPUS)

Inactive:

Lactose Sugar Base to Preserve Remedy

Uses:

Use the leaflet enclosed for detail.

Uses:

Use the leaflet enclosed for detail.

KEEP OUT OF REACH OF CHILDREN

Warnings and Storage:

Ask a professional before use if pregnant or breast feeding or if you have severe symptoms. Keep away from children. If you have a reaction to this product that is not positive, discontinue use.

Store in a cool and dry place.

Packaging:

30gm jar standard quality packing.

Warnings and Storage:

Ask a professional before use if pregnant or breast feeding or if you have severe symptoms. Keep away from children. If you have a reaction to this product that is not positive, discontinue use.

Store in a cool and dry place.

Packaging:

30gm jar standard quality packing.

Entire package label